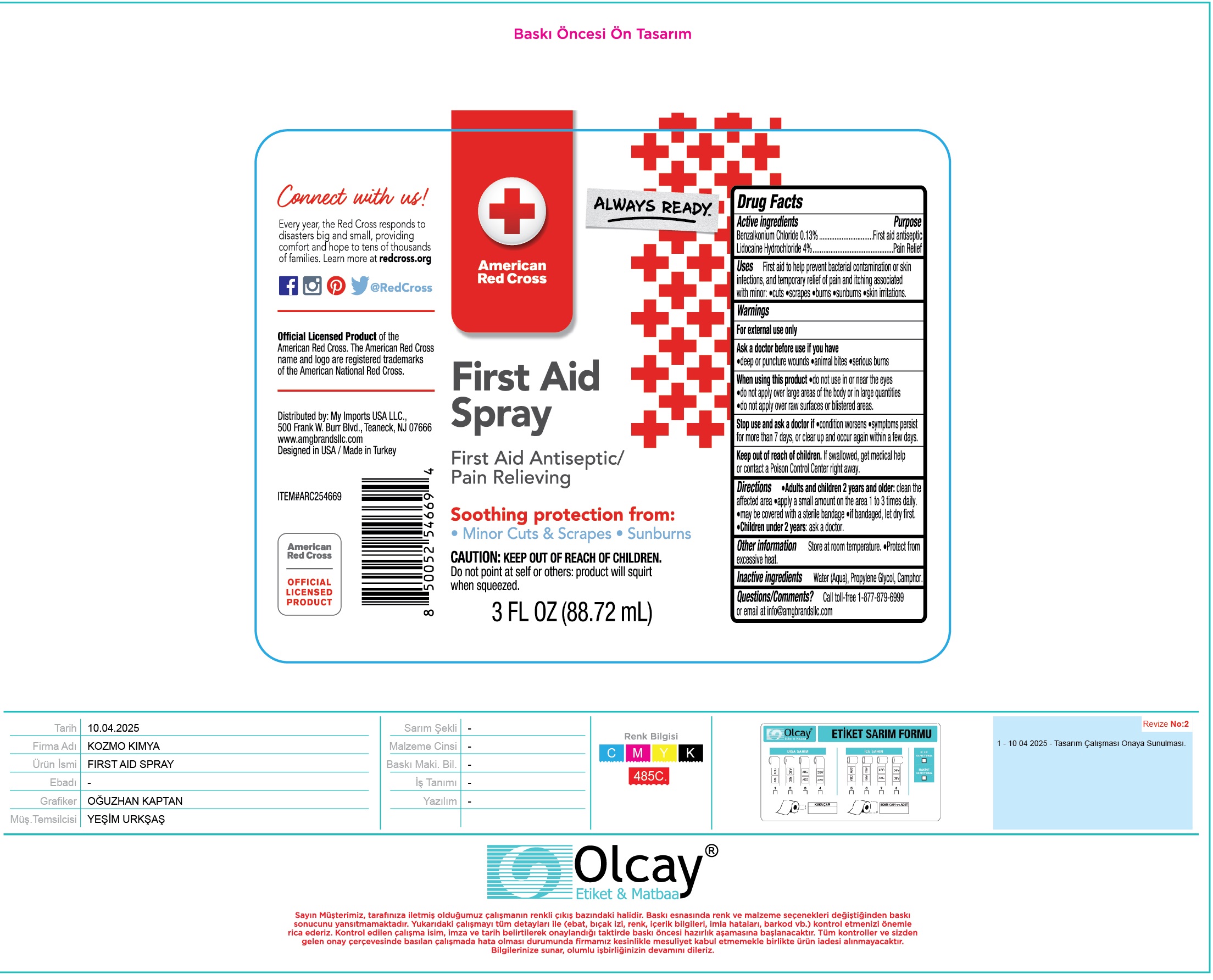 DRUG LABEL: American Red Cross First Aid
NDC: 51628-0368 | Form: SPRAY
Manufacturer: MY IMPORTS USA, LLC
Category: otc | Type: HUMAN OTC DRUG LABEL
Date: 20250501

ACTIVE INGREDIENTS: BENZALKONIUM CHLORIDE 1.3 mg/1 mL; LIDOCAINE HYDROCHLORIDE 40 mg/1 mL
INACTIVE INGREDIENTS: WATER; PROPYLENE GLYCOL; CAMPHOR (SYNTHETIC)

American Red Cross First Aid Spray

Active ingredients

Benzalkonium Chloride 0.13%
Lidocaine Hydrochloride 4%

Purpose

First aid antiseptic
Pain Relief

Uses

First aid to help prevent bacterial contamination or skin infections, and temporary relief of pain and itching associated with minor: • cuts•scrapes • burns • sunburns • skin irritations.

Warnings

For external use only

Ask a doctor before use if you have

• deep or puncture wounds • animal bites • serious burns

When using this product

- do not use in or near the eyes
- do not apply over large areas of the body or in large quantities
- do not apply over raw surfaces or blistered areas.

Stop use and ask a doctor if

• condition worsens • symptoms persist for more than 7 days, or clear up and occur again within a few days.

Keep out of reach of children.

If swallowed, get medical help or contact a Poison Control Center right away.

Directions

- Adults and children 2 years and older:clean the affected area • apply a small amount on the area 1 to 3 times daily. • may be covered with a sterile bandage • if bandaged, let dry first.
- Children under 2 years:ask a doctor.

Other information

Store at room temperature. • Protect from excessive heat.

Inactive ingredients

Water (Aqua), Propylene Glycol, Camphor.

Questions/Comments?

Call toll-free 1-877-879-6999
or email at info@amgbrandsllc.com